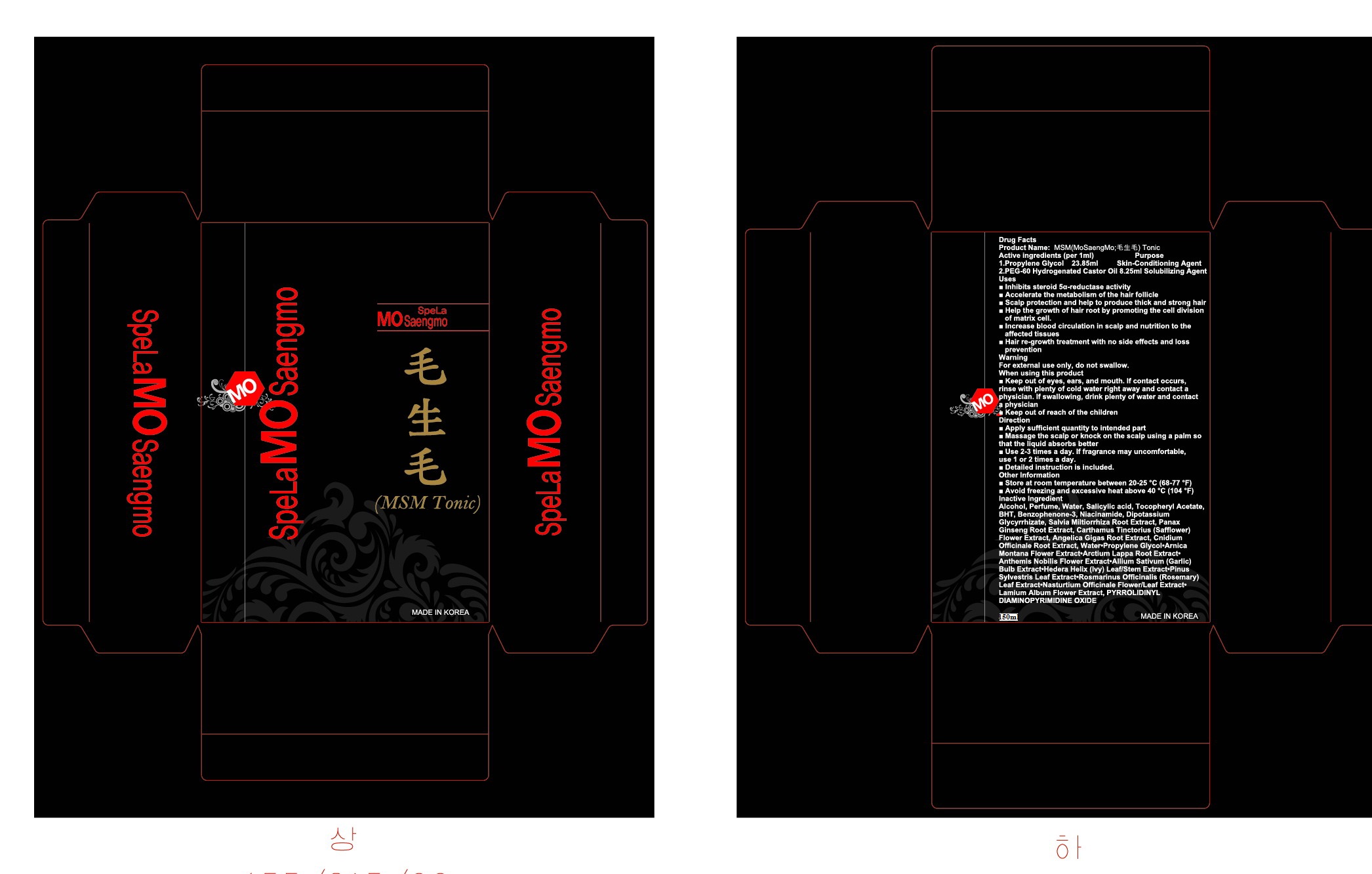 DRUG LABEL: MSM (MoSaengMo)
NDC: 76369-5001 | Form: LIQUID
Manufacturer: Handock Cosmetics Inc
Category: otc | Type: HUMAN OTC DRUG LABEL
Date: 20111111

ACTIVE INGREDIENTS: PROPYLENE GLYCOL 23.85 mL/150 mL
INACTIVE INGREDIENTS: ALCOHOL; WATER; SALICYLIC ACID; TOCOPHEROL; BUTYLATED HYDROXYTOLUENE; DIOXYBENZONE; NIACINAMIDE; GLYCYRRHIZINATE DIPOTASSIUM; SALVIA MILTIORRHIZA ROOT; PANAX GINSENG ROOT WATER; SAFFLOWER; ANGELICA GIGAS ROOT; CNIDIUM OFFICINALE ROOT; ARNICA MONTANA FLOWER; ARCTIUM LAPPA ROOT; CHAMAEMELUM NOBILE FLOWER; GARLIC; HEDERA HELIX LEAF; PINE NEEDLE OIL (PINUS SYLVESTRIS); ROSEMARY; LAMIUM ALBUM FLOWER; POLYOXYL 60 HYDROGENATED CASTOR OIL; HEDERA HELIX FLOWERING TWIG

Drug Facts

active ingredient: propylene glycol

inactive ingredient: Alcohol, Perfume, Water, Salicylic acid, Tocopheryl Acetate, BHT, Benzophenone-3, Niacinamide, Dipotassium Glycyrrhizate, Salvia Miltiorrhiza Root Extract, Panax Ginseng Root Extract, Carthamus Tinctorius (Safflower) Flower Extract, Angelica Gigas Root Extract, Cnidium Officinale Root Extract, Water·Propylene Glycol·Arnica Montana Flower Extract·Arctium Lappa Root Extract·Anthemis Nobilis Flower Extract·Allium Sativum (Garlic) Bulb Extract·Hedera Helix (Ivy) Leaf/Stem Extract·Pinus Sylvestris Leaf Extract·Rosmarinus Officinalis (Rosemary) Leaf Extract·Nasturtium Officinale Flower/Leaf Extract·Lamium Album Flower Extract, PYRROLIDINYL DIAMINOPYRIMIDINE OXIDE

PURPOSE

■ Inhibits steroid 5α-reductase activity
■ Accelerate the metabolism of the hair follicle
■ Scalp protection and help to produce thick and strong hair
■ Help the growth of hair root by promoting the cell division of matrix cell.
■ Increase blood circulation in scalp and nutrition to the affected tissues
■ Hair re-growth treatment with no side effects and loss prevention

keep out of reach of the children

INDICATIONS AND USAGE

■ Apply sufficient quantity to intended part
■ Massage the scalp or knock on the scalp using a palm so that the liquid absorbs better
■ Use 2-3 times a day. If fragrance may uncomfortable, use 1 or 2 times a day.

WARNINGS

For external use only, Do not swallow
When using this product
■ Keep out of eyes, ears, and mouth. If contact occurs, rinse with plenty of cold water right away and contact a physician. If swallowing, drink plenty of water and contact a physician

DOSAGE AND ADMINISTRATION

■ For best results, use with MSM shampoo together